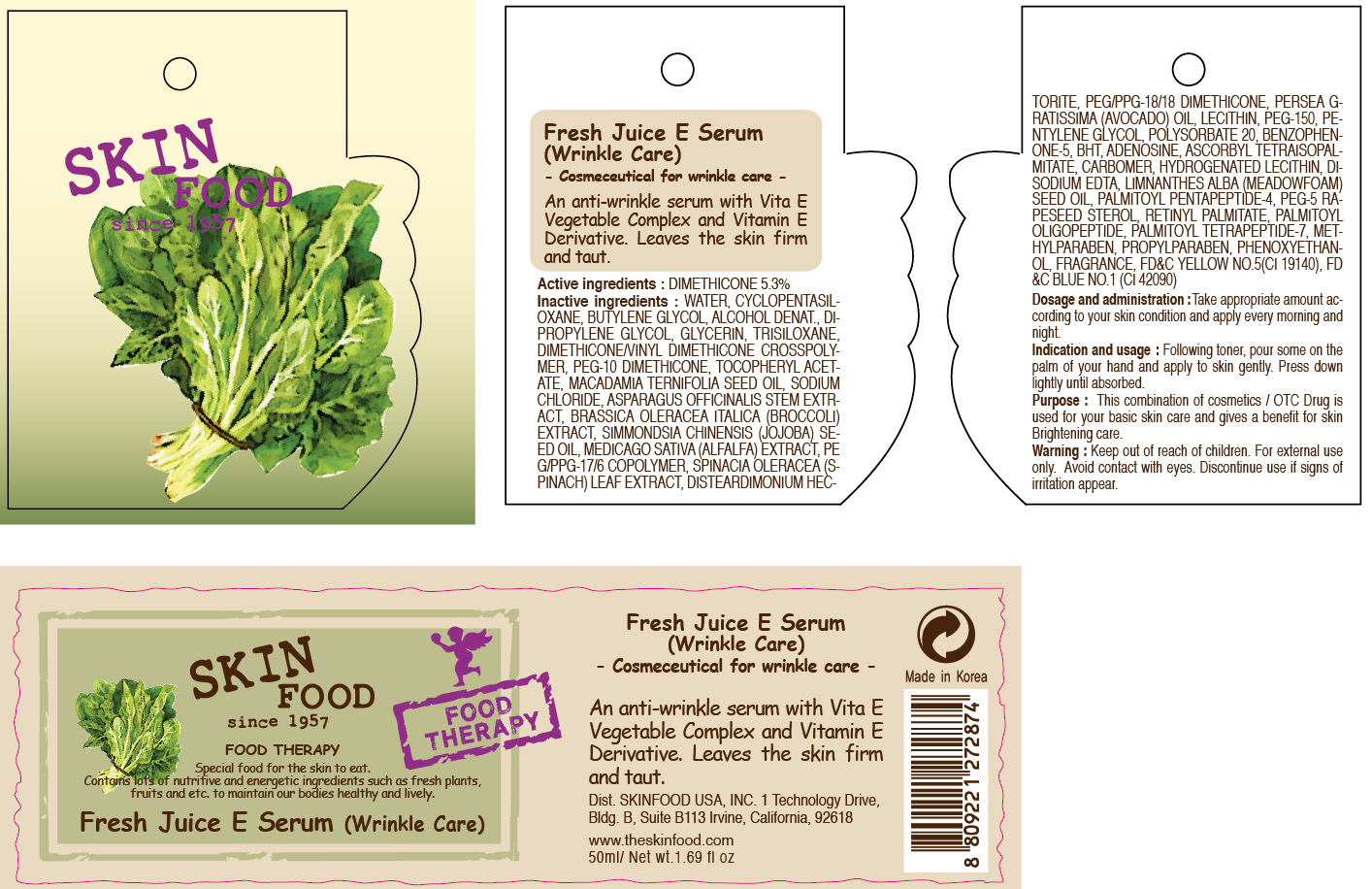 DRUG LABEL: FRESH JUICE E SERUM
NDC: 76214-024 | Form: CREAM
Manufacturer: SKINFOOD CO., LTD.
Category: otc | Type: HUMAN OTC DRUG LABEL
Date: 20110922

ACTIVE INGREDIENTS: DIMETHICONE 2.65 mL/50 mL
INACTIVE INGREDIENTS: WATER; CYCLOMETHICONE 5; BUTYLENE GLYCOL; DIPROPYLENE GLYCOL; GLYCERIN; TRISILOXANE; MACADAMIA OIL; SODIUM CHLORIDE; ASPARAGUS; BROCCOLI; ALFALFA SEED; SPINACH; PHENOXYETHANOL; METHYLPARABEN; AVOCADO OIL; LECITHIN, SOYBEAN; POLYETHYLENE GLYCOL 7000; PENTYLENE GLYCOL; POLYSORBATE 20; PROPYLPARABEN; BUTYLATED HYDROXYTOLUENE; ADENOSINE; HYDROGENATED SOYBEAN LECITHIN; EDETATE DISODIUM; MEADOWFOAM SEED OIL; PALMITOYL PENTAPEPTIDE-4; PALMITOYL OLIGOPEPTIDE; PALMITOYL TETRAPEPTIDE-7

Drug Facts

Active ingredient: DIMETHICONE 5.3%

Inactive ingredients:
WATER, CYCLOPENTASILOXANE, BUTYLENE GLYCOL, ALCOHOL DENAT., DIPROPYLENE GLYCOL, GLYCERIN, TRISILOXANE, DIMETHICONE/VINYL DIMETHICONE CROSSPOLYMER, PEG-10 DIMETHICONE, TOCOPHERYL ACETATE, MACADAMIA TERNIFOLIA SEED OIL, SODIUM CHLORIDE, ASPARAGUS OFFICINALIS STEM EXTRACT, BRASSICA OLERACEA ITALICA (BROCCOLI) EXTRACT, SIMMONDSIA CHINENSIS (JOJOBA) SEED OIL, MEDICAGO SATIVA (ALFALFA) EXTRACT, PEG/PPG-17/6 COPOLYMER, SPINACIA OLERACEA (SPINACH) LEAF EXTRACT, DISTEARDIMONIUM HECTORITE, PEG/PPG-18/18 DIMETHICONE, PERSEA GRATISSIMA (AVOCADO) OIL, LECITHIN, PEG-150, PENTYLENE GLYCOL, POLYSORBATE 20, BENZOPHENONE-5, BHT, ADENOSINE, ASCORBYL TETRAISOPALMITATE, CARBOMER, HYDROGENATED LECITHIN, DISODIUM EDTA, LIMNANTHES ALBA (MEADOWFOAM) SEED OIL, PALMITOYL PENTAPEPTIDE-4, PEG-5 RAPESEED STEROL, RETINYL PALMITATE, PALMITOYL OLIGOPEPTIDE, PALMITOYL TETRAPEPTIDE-7, METHYLPARABEN, PROPYLPARABEN, PHENOXYETHANOL, FRAGRANCE

PURPOSE

Purpose: This combination of cosmetics / OTC Drug is used for your basic skin care and gives a benefit for skin Brightening care.

Warnings:
For external use only.
Avoid contact with eyes.
Discontinue use if signs of irritation appear.

Keep out of reach of children:
Keep out of reach of children.

Indication and usage:
Following toner, pour some on the palm of your hand and apply to skin gently.
Press down lightly until absorbed.

Dosage and administration:
Take appropriate amount according to your skin condition and apply every morning and night.